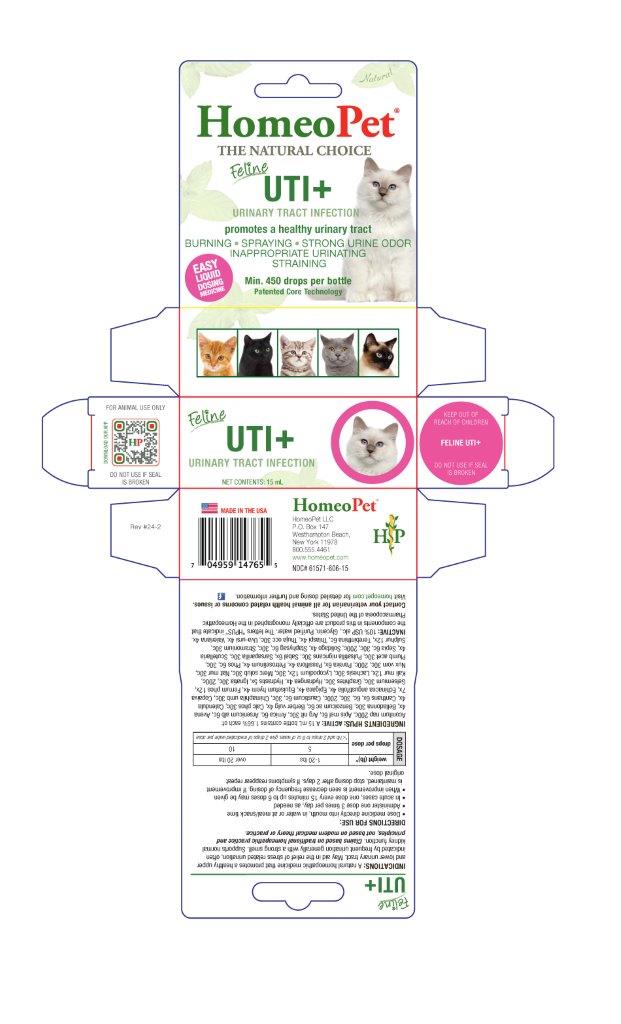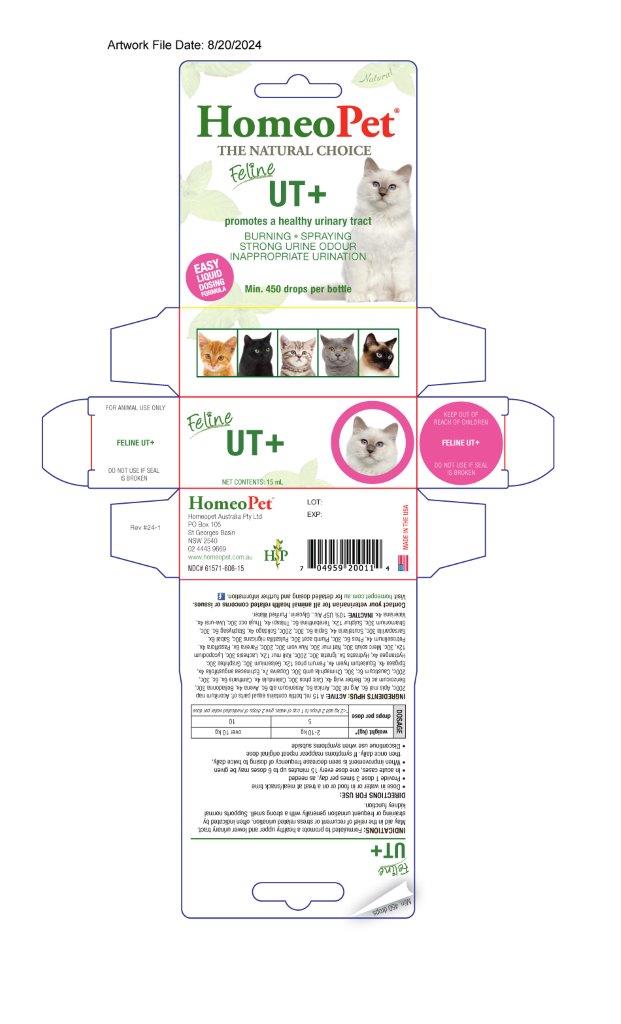 DRUG LABEL: UTI
NDC: 61571-606 | Form: LIQUID
Manufacturer: HomeoPet, LLC
Category: homeopathic | Type: OTC ANIMAL DRUG LABEL
Date: 20251211

ACTIVE INGREDIENTS: ACONITUM NAPELLUS 200 [hp_C]/15 mL; APIS MELLIFERA 6 [hp_C]/15 mL; SILVER NITRATE 30 [hp_C]/15 mL; ARNICA MONTANA 6 [hp_C]/15 mL; ARSENIC TRIOXIDE 6 [hp_C]/15 mL; AVENA SATIVA FLOWERING TOP 4 [hp_X]/15 mL; ATROPA BELLADONNA 30 [hp_C]/15 mL; BENZOIC ACID 6 [hp_C]/15 mL; BERBERIS VULGARIS ROOT BARK 4 [hp_X]/15 mL; CALCIUM PHOSPHATE 30 [hp_C]/15 mL; CALENDULA OFFICINALIS FLOWERING TOP 4 [hp_X]/15 mL; LYTTA VESICATORIA 6 [hp_X]/15 mL; CAUSTICUM 6 [hp_C]/15 mL; CHIMAPHILA UMBELLATA 30 [hp_C]/15 mL; COPAIFERA OFFICINALIS RESIN 7 [hp_X]/15 mL; ECHINACEA ANGUSTIFOLIA 4 [hp_X]/15 mL; EPIGAEA REPENS 4 [hp_X]/15 mL; EQUISETUM HYEMALE 4 [hp_X]/15 mL; FERRUM PHOSPHORICUM 12 [hp_X]/15 mL; GELSEMIUM SEMPERVIRENS ROOT 30 [hp_C]/15 mL; GRAPHITE 30 [hp_C]/15 mL; HYDRANGEA ARBORESCENS ROOT 4 [hp_X]/15 mL; GOLDENSEAL 5 [hp_X]/15 mL; STRYCHNOS IGNATII SEED 30 [hp_C]/15 mL; POTASSIUM CHLORIDE 12 [hp_X]/15 mL; LACHESIS MUTA VENOM 30 [hp_C]/15 mL; LYCOPODIUM CLAVATUM SPORE 12 [hp_X]/15 mL; MERCURIUS SOLUBILIS 30 [hp_C]/15 mL; SODIUM CHLORIDE 30 [hp_C]/15 mL; STRYCHNOS NUX-VOMICA SEED 30 [hp_C]/15 mL; CHONDRODENDRON TOMENTOSUM ROOT 6 [hp_X]/15 mL; PASSIFLORA INCARNATA FLOWERING TOP 4 [hp_X]/15 mL; PETROSELINUM CRISPUM 4 [hp_X]/15 mL; PHOSPHORUS 6 [hp_C]/15 mL; LEAD ACETATE ANHYDROUS 30 [hp_C]/15 mL; PULSATILLA PRATENSIS 30 [hp_C]/15 mL; SAW PALMETTO 6 [hp_X]/15 mL; SARSAPARILLA 30 [hp_C]/15 mL; SCUTELLARIA LATERIFLORA 4 [hp_X]/15 mL; SEPIA OFFICINALIS JUICE 6 [hp_C]/15 mL; SOLIDAGO VIRGAUREA FLOWERING TOP 4 [hp_X]/15 mL; DELPHINIUM STAPHISAGRIA SEED 6 [hp_C]/15 mL; DATURA STRAMONIUM 30 [hp_C]/15 mL; SULFUR 12 [hp_X]/15 mL; TURPENTINE 6 [hp_C]/15 mL; CAPSELLA BURSA-PASTORIS 4 [hp_X]/15 mL; THUJA OCCIDENTALIS LEAFY TWIG 30 [hp_C]/15 mL; ARCTOSTAPHYLOS UVA-URSI LEAF 4 [hp_X]/15 mL; VALERIAN 4 [hp_X]/15 mL
INACTIVE INGREDIENTS: ALCOHOL; WATER; GLYCERIN

UTI

INDICATIONS

A natural homeopathic medicine that promotes a healthy upper and lower urinary tract. May aid in the relief of stress urination, often indicated by frequent urination generally with a strong smell. Supports normal kidney function. Claims based on traditional homeopathic practice and principles, not based on modern medical theory or practice.

DIRECTIONS FOR USE AND DOSAGE

Oral remedy, can be dosed directly into mouth, in water or at meal/snack time
Administer one dose 3 times per day, as needed
In acute cases, one dose every 15 minutes up to 6 doses may be given
When improvement is seen decrease frequency of dosing. If improvement is maintained, stop dosing after 2 days. If symptoms reappear repeat orginal dose

Dosage | weight (lb)* | 1-20 lbs | over 20 lbs
Dosage | drops per dose | 5 | 10
Dosage | *<1 lb add 2 drops to 8 oz of water, give 2 drops of medicated water per dose

INGREDIENTS HPUS: ACTIVE

Aconitum nap 200c, Apis mel 6c, Arg nit 30c, Arnica 6c, Arsenicum alb 6c, Avena 4x, Belladonna 30c, Benzoicumm ac 6c, Berber vulg 4x, Calc phos 30c, Calendula 4x, Cantharis 6x, 6c, 30c, 200c, Causticum 6c, 30c, Chimaphila umb 30c, Copaiva 7x, Echinacea angustifolia 4x, Epigaea 4x, Equisetum hyem 4x, Ferrum phos 12x, Gelsemium 30c, Graphites 30c, Hydrangea 4x, Hydrastis 5x, Ignatia 30c, 200c, Kali mur 12x, Lachesis 30c, Lycopodium 12x, 30c, Merc solub 30c, Nat mur 30c, Nux vom30c, 200c, Pareira 6x, Passiflora 4x, Petroselinum 4x, Phos 6c, 30c, Plumb acet 30c, Pulsatilla 30c, Sabal 6x, Sarsaparilla 30c, Scutellaria 4x, Sepia 6c, 30c, 200c, Solidago 4x, Staphysag 6c, 30c, Stramonium 30c, Sulphur 12x, Terebinthina 6c, Thlaspi 4x, Thuja occ 30c, Uva-ursi 4x, Valeriana 4x.

INACTIVE INGREDIENTS

USP Alcohol, Glycern, Purified Water

ASK DOCTOR

Contact your veterinarian for all animal health related concerns or issues.